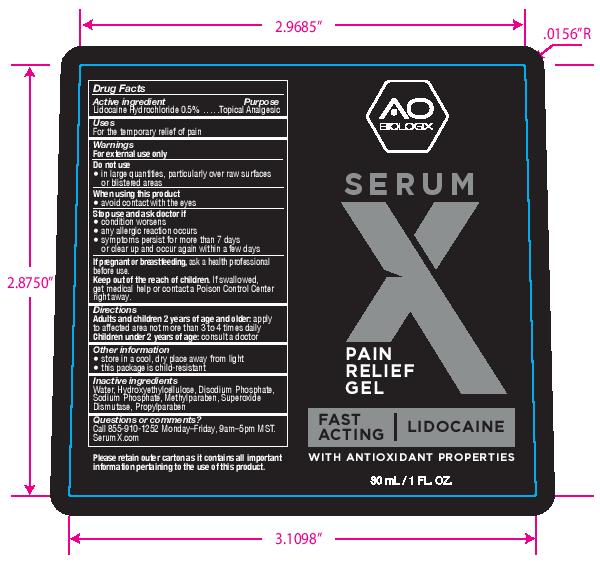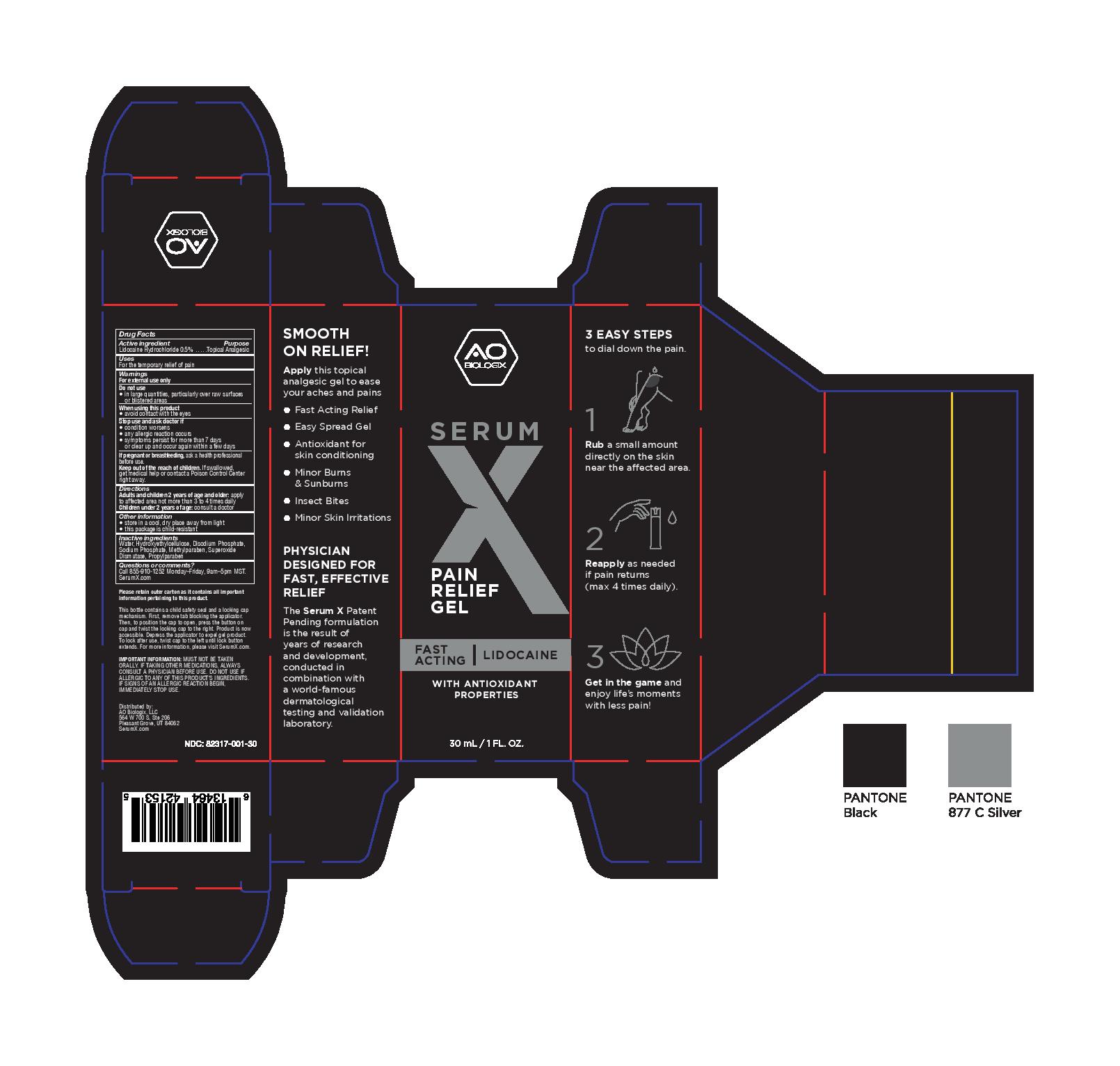 DRUG LABEL: Serum X
NDC: 82317-001 | Form: GEL
Manufacturer: AO Biologix, LLC
Category: otc | Type: HUMAN OTC DRUG LABEL
Date: 20241211

ACTIVE INGREDIENTS: LIDOCAINE HYDROCHLORIDE 0.5 g/100 g
INACTIVE INGREDIENTS: HYDROXYETHYL CELLULOSE, UNSPECIFIED; SODIUM PHOSPHATE; PROPYLPARABEN; WATER; METHYLPARABEN; SODIUM PHOSPHATE, DIBASIC, ANHYDROUS; SUPEROXIDE DISMUTASE (SACCHAROMYCES CEREVISIAE)

Serum X Pain Relief Gel

Active ingredient

Lidocaine Hydrochloride 0.5%

Purpose

Lidocaine Hydrochloride 0.5%...............Topical Analgesic

Uses

For the temporary relief of pain

Warnings

For external use only

Do not use

- in large quantities, particularly over raw surfaces or blistered areas

When using this product

- avoid contact with the eyes

Stop use and ask doctor if

- condition worsens
- any allergic reaction occurs
- symptoms persist for more than 7 days or clear up and occur again within a few days

PREGNANCY OR BREAST FEEDING

If pregnant or breastfeeding,ask a health professional before use.

KEEP OUT OF REACH OF CHILDREN

Keep out of the reacho f children.If swallowed, get medical help or contact a Poison Control Center right away.

Directions

Adults and children 2 years of age and older:apply to affected area not more than 3 to 4 times daily

Children under 2 years of age:consult a doctor

Other information

- store in a cool, dry place away from light
- this package is child-resistant

Inactive ingredients

Water, Hydroxyethylcellulose, Disodium Phosphate, Sodium Phosphate, Methylparaben, Superoxide Dismutase, Propylparaben

Questions or comments?

Call 855-910-1252 Monday-Friday; 9am-5pm MST.

SerumX.com

PACKAGE LABEL

AO Biologix

Serum X

Pain Relief Gel

Fast Acting Lidocaine

With Antioxidant Properties

30mL/1 Fl. oz.